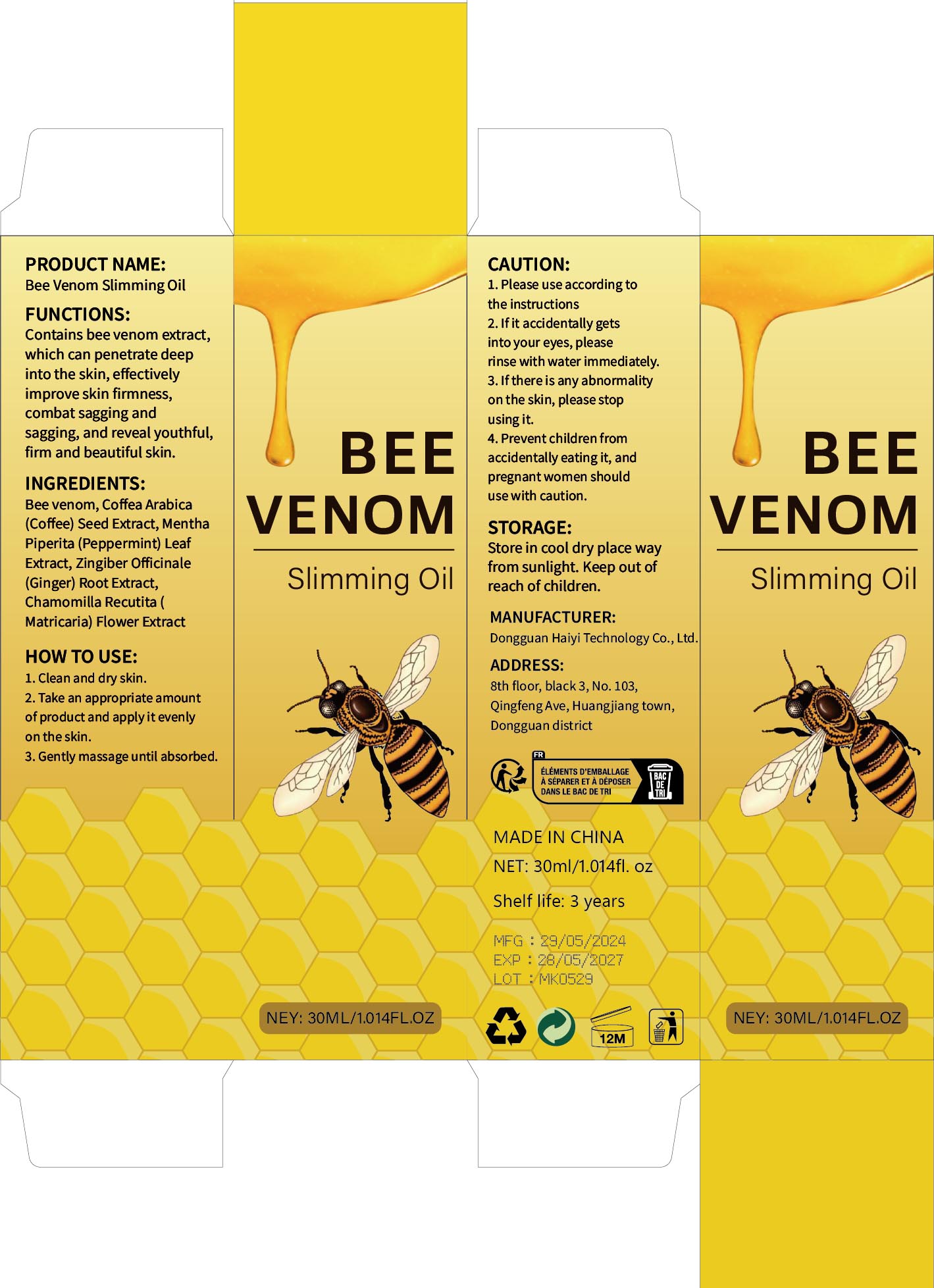 DRUG LABEL: Bee venom slimming Oil
NDC: 84732-068 | Form: OIL
Manufacturer: Dongguan Haiyi Technology Co.,Ltd.
Category: otc | Type: HUMAN OTC DRUG LABEL
Date: 20241026

ACTIVE INGREDIENTS: APIS MELLIFERA VENOM 1 mg/100 mL
INACTIVE INGREDIENTS: COFFEA ARABICA (COFFEE) SEED EXTRACT; MENTHA PIPERITA (PEPPERMINT) LEAF EXTRACT; GINGER; CHAMOMILE

Active ingredient

Bee venom

Inactive ingredient

Coffea Arabica(Coffee) Seed Extract, MenthaPiperita (Peppermint) Leaf Extract, Zingiber Officinale(Ginger) Root Extract,Chamomilla Recutita (Matricaria) Flower Extract

Purpose section

Contains bee venom extract,which can penetrate deepinto the skin, effectivelyimprove skin firmness,combat sagging andsagging, and reveal youthful,firm and beautiful skin.

Warning

1).For external use only, avoid directcontact with eyes, lf you feel any
discomfort, stop using itand wash it with plenty of water. In severe cases,
pleaseseek medical attention in time.
2). Not allowed to be used ondamaged skin,

stop use

This product may cause allergic reactions in asmall number of people.
lf youexperience any discomfort,please stop using it immediately.

not use

Not suitable for use by children, pregnantor breast feeding people.

OUT OF CHILDREN

KEEP THE PRODUCT OUT OF REACH OF CHILDREN to

HOW TO USE

1. Clean and dry skin.

2. Take an appropriate amountof product and applyit evenlyon the skin.

3. Gently massage until absorbed.

Dosage

take an appropriateamount,Use 2-3 times a week